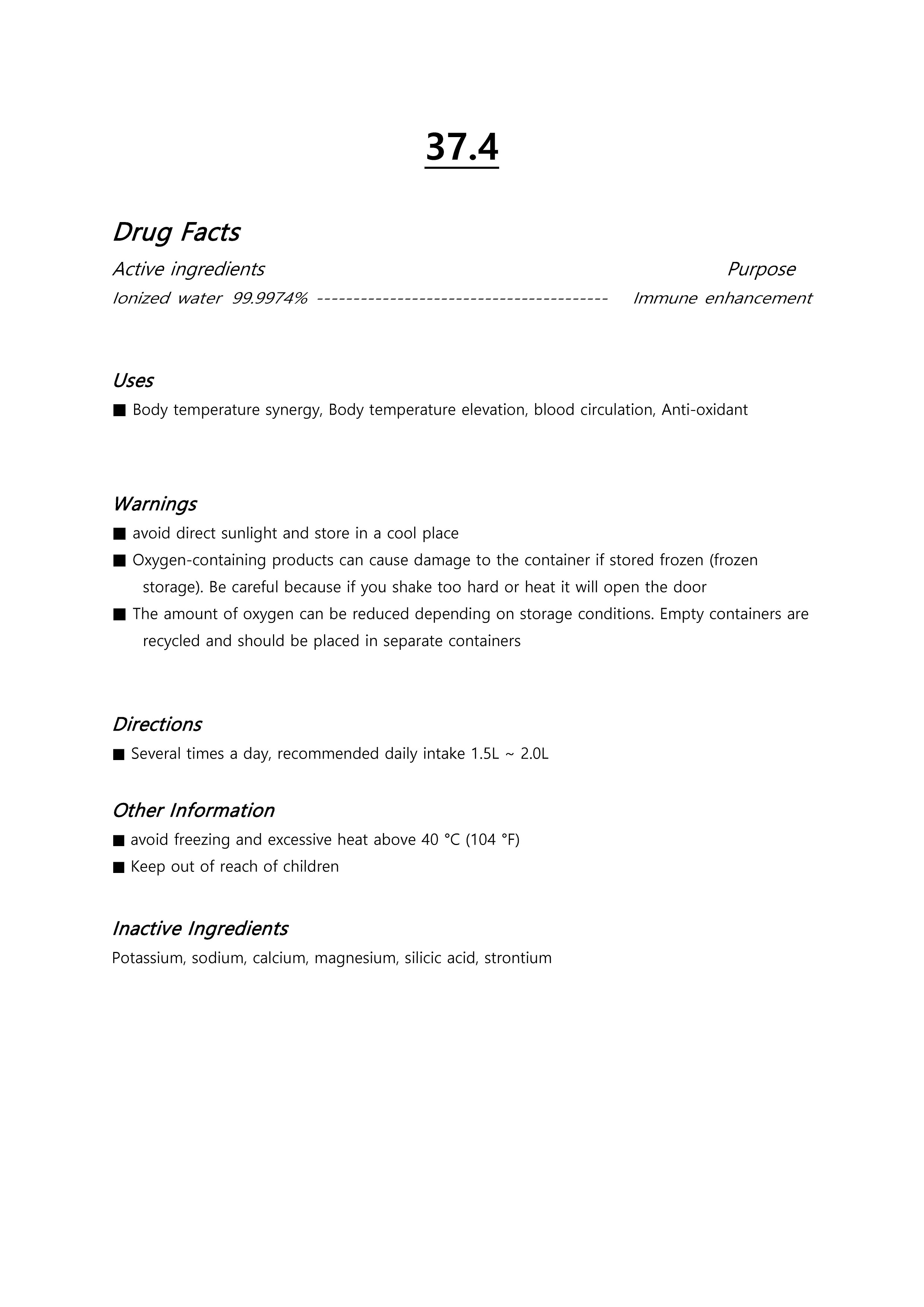 DRUG LABEL: 37.4
NDC: 71631-0004 | Form: LIQUID
Manufacturer: Jesus Glory Bio Co.,Ltd.
Category: otc | Type: HUMAN OTC DRUG LABEL
Date: 20220126

ACTIVE INGREDIENTS: WATER 99.9974 g/100 L
INACTIVE INGREDIENTS: OXYGEN

Drug Facts

ACTIVE INGREDIENT

Water

INACTIVE INGREDIENT

Oxygen

PURPOSE

To help the treatment and prevention of blood circulation, antioxidant

keep out of reach of the children

INDICATIONS AND USAGE

take 100ml each time

WARNINGS

Avoid direct sunlight and store in a cool place.
Zone Due to the nature of the product containing oxygen, the container may be damaged if it is frozen (stored frozen).
Be careful because if you shake too hard or apply heat, the lid may open.

DOSAGE AND ADMINISTRATION

for oral use only